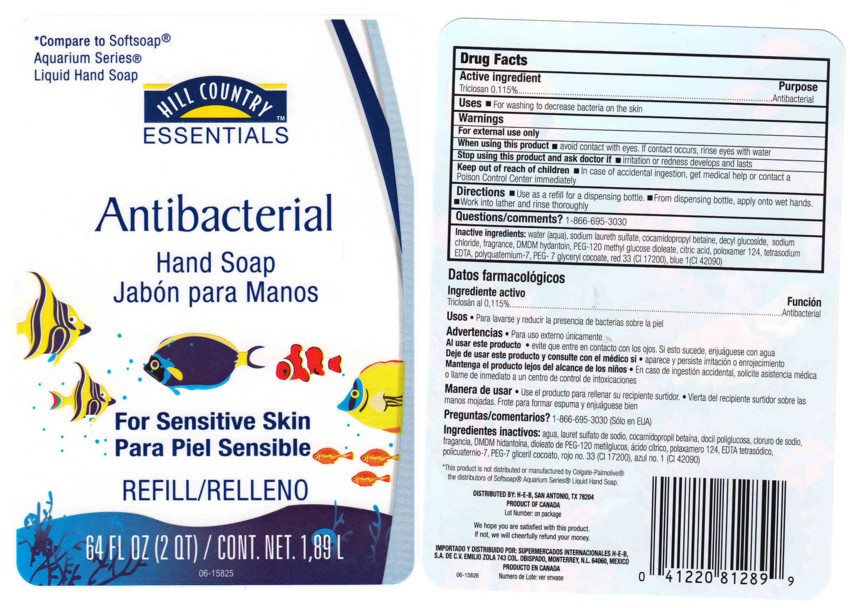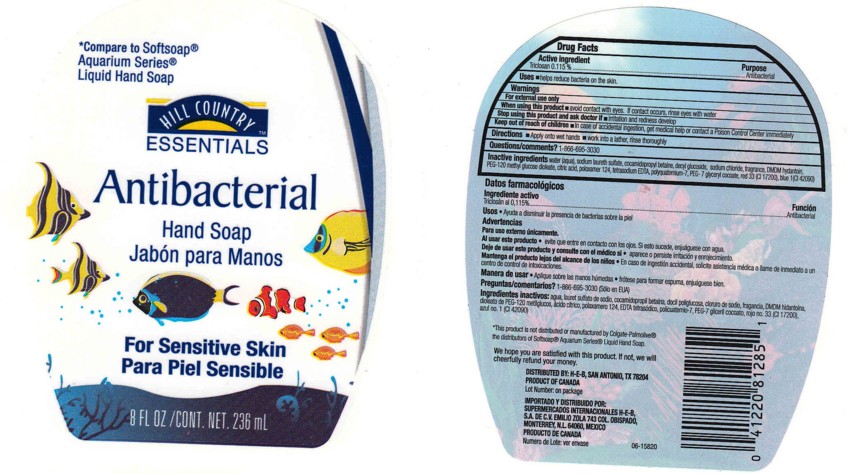 DRUG LABEL: ANTIBACTERIAL HAND SOAP
NDC: 37808-720 | Form: LOTION/SHAMPOO
Manufacturer: HEB
Category: otc | Type: HUMAN OTC DRUG LABEL
Date: 20100308

ACTIVE INGREDIENTS: TRICLOSAN 0.1150 mL/100 mL

Antibacterial Hand Soap For Sensitive Skin

ACTIVE INGREDIENT

Triclosan 0.115 % ............. (Antibacterial)

USES

For washing to decrease bacteria on the skin

WARNINGS

For external use only

STOP USING THIS PRODUCT AND ASK A DOCTOR IF

- irritation or redness develops and lasts

WHEN USING THIS PRODUCT

- Avoid contact with eyes
- If contact occurs, rinse eyes throughly with water

KEEP OUT OF REACH OF CHILDREN

- In case of accidental ingestion, get medical help or contact a Poison Control Center immediately

PACKAGE FRONT AND BACK LABELS

- 64OZ FRONT AND BACK LABELS: hce64.jpg
- 8OZ FRONT AND BACK LABELS: hce8.jpg